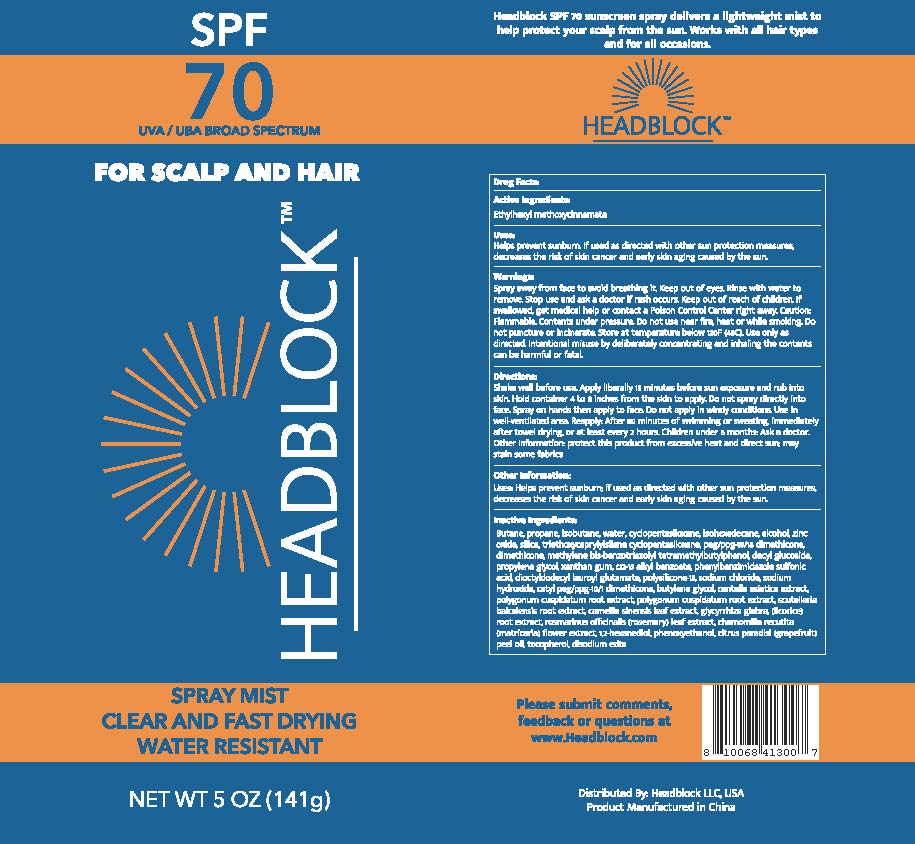 DRUG LABEL: sunscreen sprays
NDC: 82080-101 | Form: SPRAY
Manufacturer: Headblock LLC
Category: otc | Type: HUMAN OTC DRUG LABEL
Date: 20210701

ACTIVE INGREDIENTS: OCTINOXATE 5 g/100 g
INACTIVE INGREDIENTS: PEG/PPG-18/18 DIMETHICONE; DIMETHICONE; BISOCTRIZOLE; ENSULIZOLE; SODIUM HYDROXIDE; CETYL PEG/PPG-10/1 DIMETHICONE (HLB 5); GREEN TEA LEAF; CENTELLA ASIATICA WHOLE; GLYCYRRHIZA GLABRA; 1,2-HEXANEDIOL; ISOHEXADECANE; ZINC OXIDE; XANTHAN GUM; ALKYL (C12-15) BENZOATE; POLYSILICONE-15; DIOCTYLDODECYL LAUROYL GLUTAMATE; SODIUM CHLORIDE; ROSEMARY; CHAMOMILE; ALCOHOL; PROPYLENE GLYCOL; PHENOXYETHANOL; GRAPEFRUIT OIL; WATER; BUTANE; PROPANE; ISOBUTANE; SILICON DIOXIDE; TRIETHOXYCAPRYLYLSILANE; CYCLOMETHICONE 5; DECYL GLUCOSIDE; BUTYLENE GLYCOL; POLYGONUM CUSPIDATUM ROOT; SCUTELLARIA BAICALENSIS ROOT; TOCOPHEROL; EDETATE DISODIUM ANHYDROUS

sunscreen sprays

sunscreen sprays

Active Ingredient(s)

ETHYLHEXYL METHOXYCINNAMATE 5% w/w. Purpose: Sunscreen

Purpose

Sunscreen, sunscreen sprays

Use

Helps prevent sunburn.If used as directed with other sun protection measures,

decreases the risk of skin cancer and early skin aging caused by the sun.

Warnings

Spray away from face to avoid breathing it. Keep out of eyes. Rinse with water to remove. Stop use and ask a doctor if rash occurs. Keep out of reach of children. If swallowed,get medical help or contact a Poison Control Center right away. Caution: Flammable. Contents under pressure. Do not use near fire, heat or while smoking. Do not puncture or incinerate.Store at temperature below 120F (48℃). Use only as directed. Intentional misuse by deliberately concentrating and inhaling the contents can be harmful or fatal.

Directions

Shake well before use. Apply liberally 15 minutes before sun exposure and rub into skin. Hold container 4 to 6 inches from the skin to apply. Do not spray directly into face. Spray on hands then apply to face. Do not apply in windy conditions. Use in well-ventilated area. Reapply: After 80 minutes of swimming or sweating, immediately after towel drying, or at least every 2 hours. Children under 6 months: Ask a doctor. Other Information: protect this product from excessive heat and direct sun; may stain some fabrics.

Other information

Uses: Helps prevent sunburn; if used as directed with other sun protection measures, decreases the risk of skin cancer and early skin aging caused by the sun.

Inactive ingredients

Butane,propane, isobutene, water, cyclopentasiloxane, isohexadecane, alcohol, zincoxide, silica, triethoxycaprylylsilane cyclopentasiloxane, peg/ppg-18/18 dimethicone, dimethicone, methylene bis-benzotriazolyl tetramethylbutylphenol, decyl glucoside, propylene glycol, xanthan gum, C12-15 alkyl benzoate, phenylbenzimidazole sulfonic acid, dioctyldodecyl lauroyl glutamate, polysilicone-15,sodium chloride, sodium hydroxide, cetyl peg/ppg -10/1 dimethicone, butylene glycol, centella asiatica extract, polygonum cuspidatum root extract, polygonum cuspidatum root extract,scutellaria baicalensis root extract,camellia sinensis leaf extract, glycyrrhiza glabra,(licorice) root extract, rosmarinus officinalis (rosemary) leaf extract, chamomilla recutita(matricaria) flower extract, 1,2-hexanediol, phenoxyethanol, citrus paradisi (grapefruit) peel oil, tocopherol,disodium edta